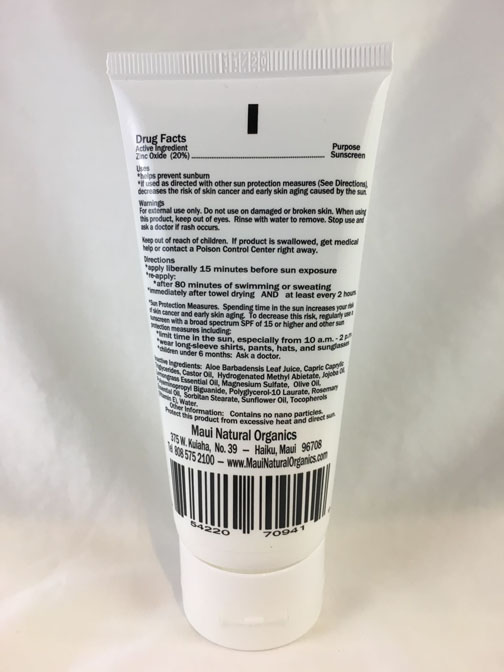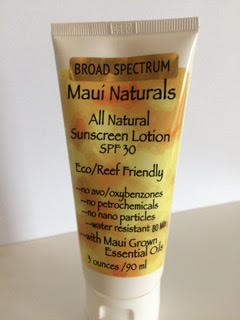 DRUG LABEL: Maui Naturals All Natural Sunscreen
NDC: 58918-002 | Form: LOTION
Manufacturer: Hawaiian Classic Perfumes, Inc.
Category: otc | Type: HUMAN OTC DRUG LABEL
Date: 20191121

ACTIVE INGREDIENTS: ZINC OXIDE 200 mg/1 mL
INACTIVE INGREDIENTS: SORBITAN MONOSTEARATE; POLYGLYCERYL-10 LAURATE; MEDIUM-CHAIN TRIGLYCERIDES; JOJOBA OIL; HYDROGENATED CASTOR OIL; MAGNESIUM SULFATE, UNSPECIFIED; OLIVE OIL; ROSEMARY OIL; WEST INDIAN LEMONGRASS OIL; HYDROGENATED METHYL ABIETATE; WATER; ALOE VERA LEAF; SUNFLOWER OIL; TOCOPHEROL; POLIHEXANIDE

Hawaiian Classic Perfumes OTC Private Label Sunscreen - Maui Naturals All Natural Sunscreen

Maui Naturals All Natural Sunscreen Lotion SPF 30

(Front Label:)

Broad Spectrum - Maui Naturals - All Natural Sunscreen SPF 30 - Eco/Reef Friendly - no avo/oxybenzones - no petrochemicals - no nano particles - water resistant - 80 Min - with Maui Grown Essential Oils - 3 ounces /90 mL

(Back Label:)

Drug Facts

Active Ingredient – Purpose

Zinc Oxide (20%) .......................................................................Sunscreen

Uses

*helps prevent sunburn

*if used as directed with other sun protection measures (See Directions), decreases the risk of skin cancer and early skin aging caused by the sun.

Warnings

For external use only. Do not use on damaged or broken skin. When using this product, keep out of eyes. Rinse with water to remove. Stop use and ask a doctor if rash occurs.

Keep out of reach of children. If product is swallowed, get medical help or contact a Poison Control Center right away.

Directions

*apply liberally 15 minutes before sun exposure

*re-apply:

*after 80 minutes of swimming or sweating

*immediately after towel drying AND at least every 2 hours.

*Sun Protection Measures. Spending time in the sun increases your risk of skin cancer and early skin aging. To decrease this risk, regularly use a sunscreen with a broad spectrum SPF of 15 or higher and other sun protection measures including:

*limit time in the sun, especially from 10 a.m. - 2 p.m.

*wear long-sleeve shirts, pants, hats, and sunglasses

*children under 6 months: Ask a doctor.

Inactive Ingredients: Aloe Barbadensis Leaf Juice, Capric Caprylic Triglycerides, Castor Oil, Hydrogenated Methyl Abietate, Jojoba Oil, Lemongrass Essential Oil, Magnesium Sulfate, Olive Oil, Polyaminopropyl Biguanide, Polyglycerol-10 Laurate, Rosemary Essential Oil, Sorbitan Stearate, Sunflower Oil, Tocopherols (Vitamin E), Water.

Other Information: Contains no nano particles.

Protect this product from excessive heat and direct sun.

Maui Natural Organics

375 W. Kuiaha, No. 39 — Haiku, Maui 96708

Tel 808 575 2100 — www.MauiNaturalOrganics.com

7 54220 70941 9